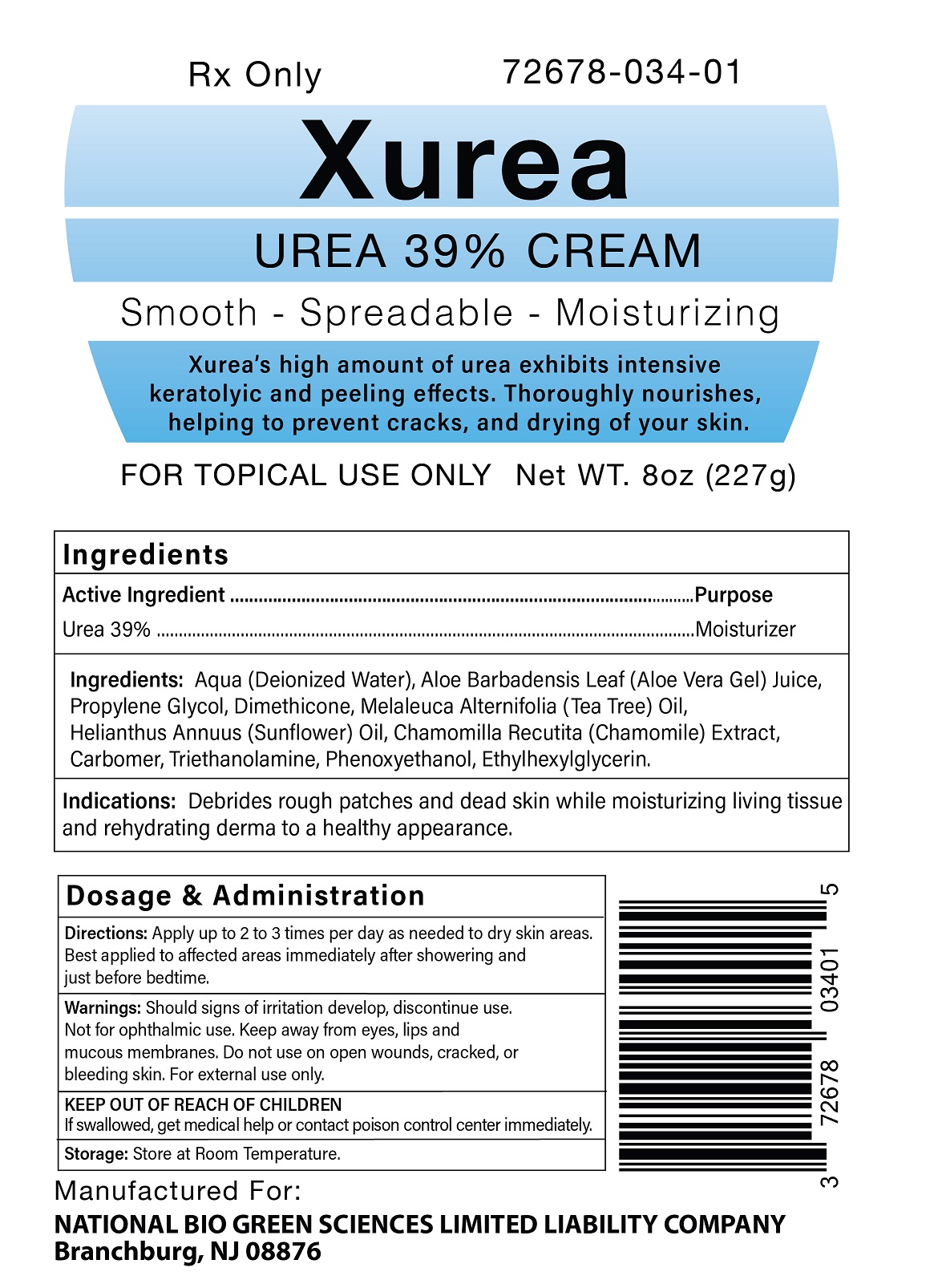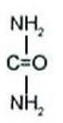 DRUG LABEL: Xurea
NDC: 72678-034 | Form: CREAM
Manufacturer: NATIONAL BIO GREEN SCIENCES LIMITED LIABILITY COMPANY
Category: prescription | Type: HUMAN PRESCRIPTION DRUG LABEL
Date: 20191011

ACTIVE INGREDIENTS: UREA 390 mg/1 g
INACTIVE INGREDIENTS: WATER; ALOE VERA LEAF; PROPYLENE GLYCOL; DIMETHICONE; MELALEUCA ALTERNIFOLIA LEAF; SUNFLOWER OIL; CHAMOMILE; CARBOMER HOMOPOLYMER, UNSPECIFIED TYPE; TROLAMINE; PHENOXYETHANOL; ETHYLHEXYLGLYCERIN

Xurea

Xurea (Urea 39% Cream) Rx only
For Topical Dermatological Use Only
Rx Only - Caution: Federal Law restricts this product to sale by, or on the order of a licensed healthcare practitioner.

Xurea Description

Xurea Cream is a potent keratolytic emollient which is a gentle, yet potent, tissue softener for skin and/or nails.
Each gram of Xurea Cream contains:
ACTIVE: 39% Urea in a cream base of:
INACTIVES: Aqua (Deionized Water), Aloe Barbadensis Leaf (Aloe Vera Gel) Juice, Propylene Glycol, Dimethicone, Melaleuca Alternifolia (Tea Tree) Oil, Helianthus Annuus (Sunflower) Oil, Chamomilla Recutita (Chamomile) Extract, Carbomer, Triethanolamine, Phenoxyethanol, Ethylhexylglycerin.

CHEMISTRY
Urea is a diamide of carbonic acid with the following chemical structure:

Xurea - Clinical Pharmacology

Urea gently dissolves the intercellular matrix which results in loosening the horny layer of skin and shedding scaly skin at regular intervals, thereby softening hyperkeratotic areas. Urea also hydrates and gently dissolves the intercellular matrix of the nail plate, which can result in the softening and eventual debridement of the nail plate.

PHARMACOKINETICS

The mechanism of action of topically applied Urea is not yet known.

INDICATIONS AND USES

For debridement and promotion of normal healing of hyperkeratotic surface lesions, particularly where healing is retarded by local infection, necrotic tissue, fibrinous or prurient debris or eschar. Urea is useful for the treatment of hyperkeratotic conditions such as dry, rough skin, dermatitis, psoriasis, xerosis, ichthyosis, eczema, keratosis, keratoderma, corns and calluses, as well as damaged, ingrown and devitalized nails.

Contraindications

Xurea Cream is contraindicated in patients with known hypersensitivity to any of the listed ingredients.

Warnings

For external use only. Avoid contact with eyes, lips or mucous membranes. Do not use on areas of broken skin.

Precautions

Stop use and ask a doctor if redness or irritation develops. After applying this medication, wash hands and unaffected areas thoroughly. If swallowed, get medical help or contact Poison Control Center right away. KEEP THIS AND ALL MEDICATION OUT OF THE REACH OF CHILDREN.

PREGNANCY

Pregnancy Category B

Animal reproduction studies have revealed no evidence of harm to the fetus, however, there are no adequate and well-controlled studies in pregnant women. Because animal reproduction studies are not always predictive of human response, Xurea Cream should be given to a pregnant woman only if clearly needed.

NURSING MOTHERS

It is not known whether or not this drug is secreted in human milk. Because many drugs are secreted in human milk, caution should be exercised when Xurea Cream is administered to a nursing woman.

Adverse Reactions

Transient stinging, burning, itching or irritation may occur and normally disappear on discontinuing the medication.

Xurea - Dosage and Administration

Apply Xurea Cream to affected skin two to three times per day as needed or as directed by a physician. Rub in until completely absorbed. Apply to diseased or damaged nail tissue two to three times per day or as directed by a physician. Best applied to affected areas immediately after showering and just before bedtime.

How is Xurea Supplied

Xurea (39% Urea Cream) is supplied in:

8oz (227gm) Jar NDC 72678-034-01

Store at 25°C (77°F); excursions permitted to 15°C - 30°C (59° - 86°F). Protect from freezing. [See USP Controlled Room Temperature.]

Manufactured for:
NATIONAL BIO GREEN SCIENCES LIMITED LIABILITY COMPANY
Branchburg, NJ 08876

Rx only

PRINCIPAL DISPLAY PANEL - 227 gm Jar Label

Rx only

NDC 72678-034-01

Xurea UREA 39% CREAM

Smooth - Spreadable - Moisturizing

Xurea’s high amount of urea exhibits intensive keratolyic and peeling effects. Thoroughly nourishes, helping to prevent cracks, and drying of your skin.

FOR TOPICAL USE ONLY

Net WT. 8OZ (227 gm)